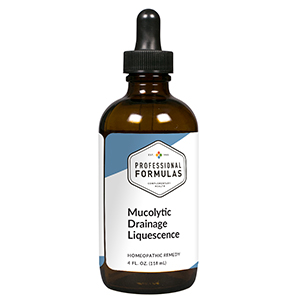 DRUG LABEL: Mucolytic Drainage Liquescence
NDC: 63083-3017 | Form: LIQUID
Manufacturer: Professional Complementary Health Formulas
Category: homeopathic | Type: HUMAN OTC DRUG LABEL
Date: 20190815

ACTIVE INGREDIENTS: PLANTAGO MAJOR WHOLE 1 [hp_X]/118 mL; URTICA DIOICA WHOLE 1 [hp_X]/118 mL; EQUISETUM ARVENSE TOP 1 [hp_X]/118 mL; EUCALYPTUS GLOBULUS LEAF 2 [hp_X]/118 mL; ASCORBIC ACID 3 [hp_X]/118 mL; EPHEDRA DISTACHYA FLOWERING TWIG 3 [hp_X]/118 mL; INULA HELENIUM ROOT 3 [hp_X]/118 mL; LOBELIA CARDINALIS WHOLE 3 [hp_X]/118 mL; PERVINCA MINOR WHOLE 3 [hp_X]/118 mL; BOS TAURUS LYMPH VESSEL 8 [hp_X]/118 mL
INACTIVE INGREDIENTS: ALCOHOL; WATER

T17

ACTIVE INGREDIENTS

Plantago major 1X
Urtica dioica 1X
Equisetum arvense 1X
Eucalyptus globulus 2X
Ascorbicum acidum 3X
Ephedra vulgaris 3X
Inula helenium 3X
Lobelia cardinalis 3X
Vinca minor 3X
Lymph 8X, 12X

QUESTIONS

Professional Formulas

PO Box 2034 Lake Oswego, OR 97035

INDICATIONS

For the temporary relief of excess mucus or fluid buildup.*

PURPOSE

*Claims based on traditional homeopathic practice, not accepted medical evidence. Not FDA evaluated.

WARNINGS

In case of overdose, get medical help or contact a poison control center right away.

Keep out of the reach of children.

PREGNANCY OR BREAST FEEDING

If pregnant or breastfeeding, ask a healthcare professional before use.

DIRECTIONS

Place drops under tongue 30 minutes before/after meals. Adults and children 12 years and over: Take one full dropper up to 2 times per day. For immediate onset of symptoms, take 10 to 15 drops every 15 minutes up to 3 hours. For less severe symptoms, take 10-15 drops hourly up to 8 hours. Consult a physician for use in children under 12 years of age.

OTHER INFORMATION

Tamper resistant. If seal is broken, do not use. After opening, close container tightly and store at room temperature away from heat.

INACTIVE INGREDIENTS

20% ethanol, purified water.

LABEL

Est 1985

Professional Formulas

Complementary Health

Mucolytic Drainage Liquescence

Homeopathic Remedy

4 FL. OZ. (118 mL)